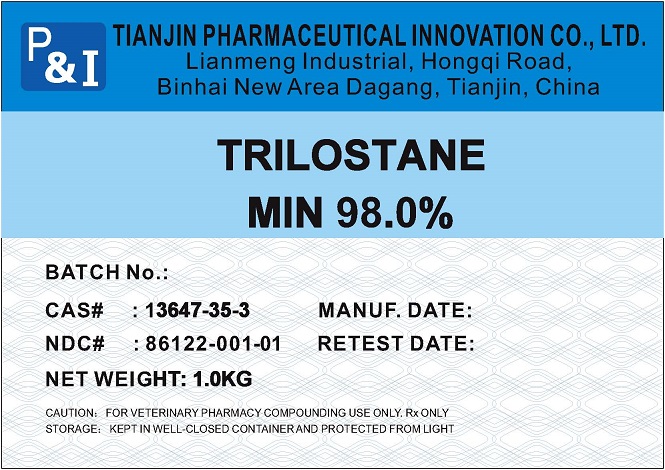 DRUG LABEL: Trilostane
NDC: 86122-001 | Form: POWDER
Manufacturer: Tianjin Pharmaceutical Innovation Co., Ltd.
Category: other | Type: BULK INGREDIENT - ANIMAL DRUG
Date: 20230104

ACTIVE INGREDIENTS: TRILOSTANE 1 kg/1 kg

Trilostane

Trilostane

TRILOSTANELISTING(2).jpg